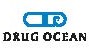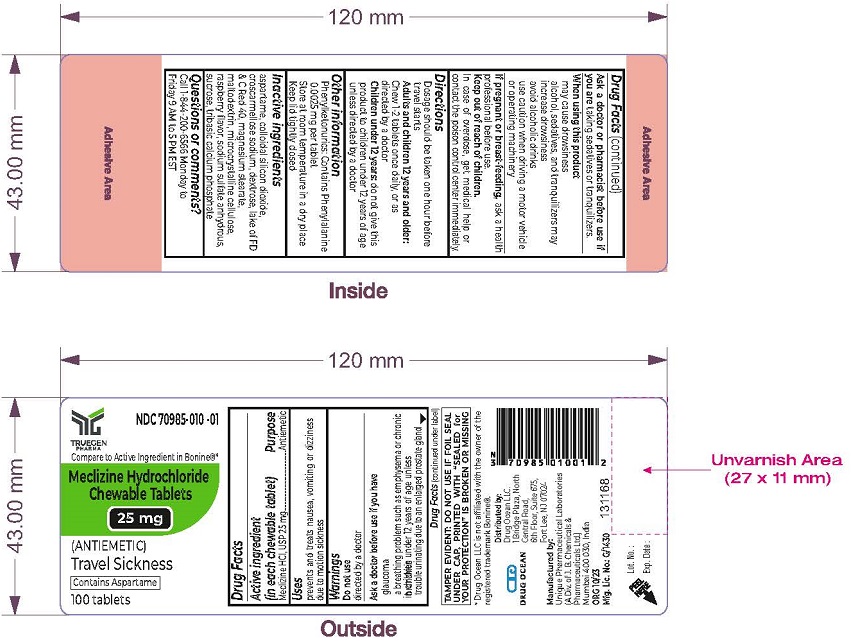 DRUG LABEL: Meclizine HCl
NDC: 70985-010 | Form: TABLET, CHEWABLE
Manufacturer: Drug Ocean LLC
Category: otc | Type: HUMAN OTC DRUG LABEL
Date: 20231223

ACTIVE INGREDIENTS: MECLIZINE HYDROCHLORIDE 25 mg/1 1
INACTIVE INGREDIENTS: SUCROSE; ASPARTAME; SILICON DIOXIDE; CROSCARMELLOSE SODIUM; DEXTROSE; FD&C RED NO. 40; TRIBASIC CALCIUM PHOSPHATE; MALTODEXTRIN; MICROCRYSTALLINE CELLULOSE; RASPBERRY; SODIUM SULFATE ANHYDROUS; MAGNESIUM STEARATE

MECLIZINE HYDROCHLORIDE CHEWABLE TABLETS 25 MG
DRUG FACTS

Active Ingredients (in each chewable tablet)

Meclizine HCl, USP 25 mg

Purpose

Antiemetic

Uses

prevents and treats nausea, vomiting or dizziness due to motion sickness.

Warnings

Do not use in children under 12 years of age unless directed by a doctor

Ask a doctor before use if you have

- glaucoma
- a breathing problem such as emphysema or chronic bronchitis
- trouble urinating due to an enlarged prostate gland

Ask a doctor or pharmacist before use if you are taking sedatives or tranquilizers.

When using this product

- may cause drowsiness
- alcohol, sedatives, and tranquilizers may increase drowsiness
- avoid alcoholic drinks
- use caution when driving a motor vehicle or operating machinery

PREGNANCY OR BREAST FEEDING

If pregnant or breast-feeding, ask a health professional before use.

Keep out of reach of children.

In case of overdose, get medical help or contact the poison control center immediately

Directions

- Dosage should be taken one hour before travel starts
- Adults and children 12 years and older: Chew 1-2 tablets once daily, or as directed by a doctor
- Children under 12 years: do not give this product to children under 12 years of age unless directed by a doctor

Other information

- Phenylketonurics: Contains Phenylalanine 0.0025 mg per tablet
- Store at room temperature in a dry place
- Keep lid tightly closed

Inactive ingredients

aspartame, colloidal silicon dioxide, croscarmellose sodium, dextrose, lake of FD & C Red 40, magnesium stearate, maltodextrin, microcrystalline cellulose, raspberry flavor, sodium sulfate anhydrous, sucrose, tribasic calcium phosphate

Questions or Comments?

Call 1-844-200-6566 Monday to Friday 9 AM to 5 PM EST

TAMPER EVIDENT: DO NOT USE IF FOIL SEAL UNDER CAP, PRINTED WITH “SEALED for YOUR PROTECTION” IS BROKEN OR MISSING

Distributed by:
Drug Ocean LLC,
1 Bridge Plaza, North Central Road

6th Floor, Suite 675

Fort Lee, NJ 07024

Manufactured by:
Unique Pharmaceutical Laboratories
(A Div. of J. B. Chemicals & Pharmaceuticals Ltd.)
Mumbai 400 030, India

ORG 12/23

PRINCIPAL DISPLAY PANEL - 25 mg Chewable Tablet Label

NDC 70985-010-01
Meclizine Hydrochloride Chewable Tablets 25mg
(ANTIEMETIC)
Travel Sickness
100 tablets